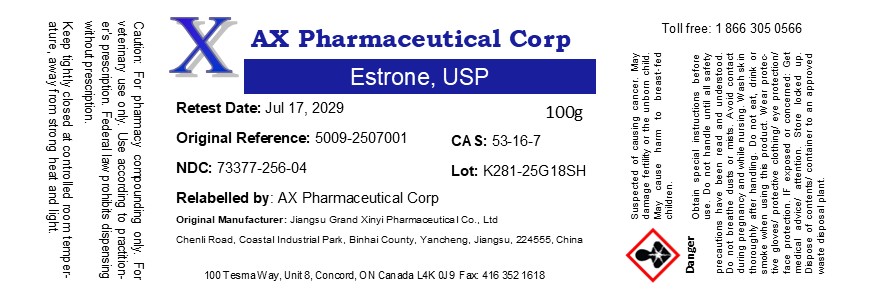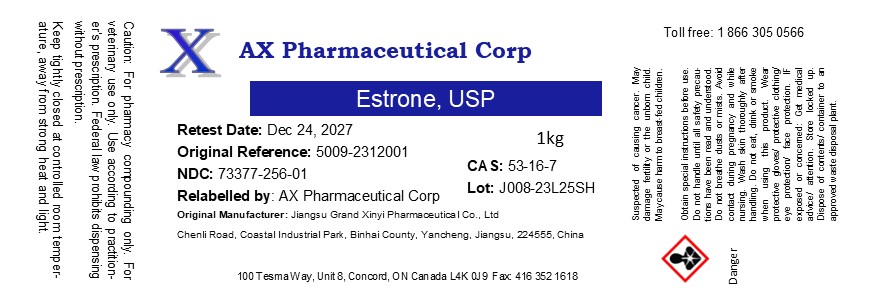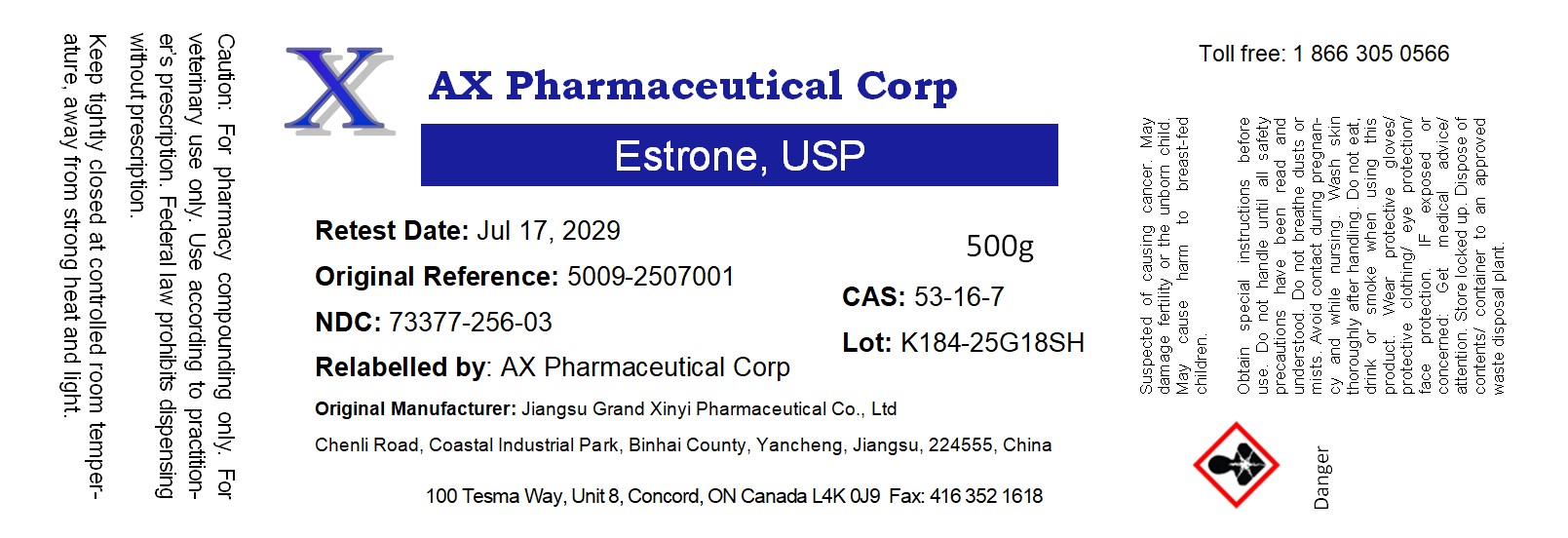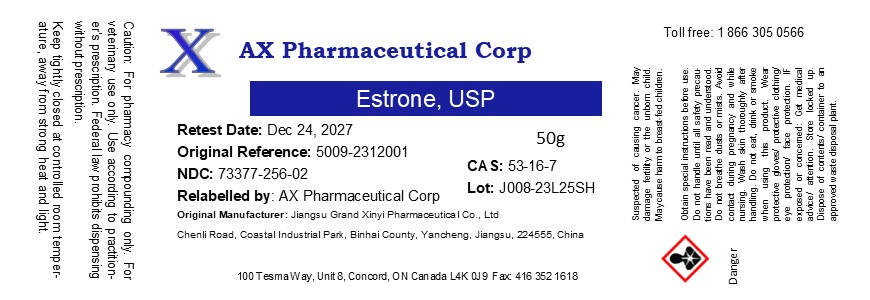 DRUG LABEL: Estrone
NDC: 73377-256 | Form: POWDER
Manufacturer: AX Pharmaceutical Corp
Category: other | Type: BULK INGREDIENT - ANIMAL DRUG
Date: 20251107

ACTIVE INGREDIENTS: Estrone 1 g/1 g

Estrone